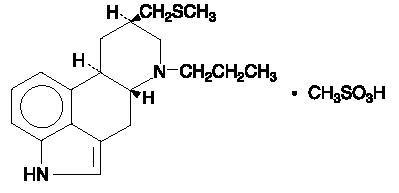 DRUG LABEL: Unknown
Manufacturer: Valeant Pharmaceuticals, Inc.
Category: prescription | Type: HUMAN PRESCRIPTION DRUG LABELING
Date: 20070330

PERMAX®
PERGOLIDE TABLETS, USP

WARNING

Cardiac Valvulopathy and Fibrotic Complications

Cardiac Valvulopathy

The use of pergolide has been shown to increase the risk of cardiac valvular disease involving one or more valves. Some patients have required valve replacement, and deaths have been reported. Cases have been reported after exposures to pergolide ranging from several months to several years. The histopathology of explanted valves is similar to that of other drug-induced valvulopathies. Precise risk estimates of pergolide-induced cardiac valvular disease are not available.

Specific risk factors predisposing patients to developing cardiac valvular disease with pergolide have not been identified. Cardiac valvulopathy has been reported with all doses of pergolide; however, available data suggest that the risk may be greater with higher doses. Doses of pergolide above 5 mg/day are not recommended (seeDOSAGE & ADMINISTRATION).

Pergolide is not recommended for use in patients with a history of cardiac valvulopathy.

Before initiating treatment with pergolide, all patients should undergo a cardiovascular evaluation, including an echocardiogram, to determine whether valvular disease is present and to provide a baseline for subsequent monitoring. Although the risk of disease progression in patients with asymptomatic valvular disease is unknown, pergolide ordinarily should not be initiated if valvulopathy is detected at screening.

All patients taking pergolide should undergo periodic echocardiograms to screen for the development of valvulopathy. Patients should also be monitored for signs and symptoms of valvulopathy, including dyspnea, edema, congestive heart failure and new cardiac murmurs. If a patient develops these signs or symptoms, consideration should be given to suspending treatment with pergolide until a full diagnostic evaluation, including echocardiogram, has been performed. Pergolide should ordinarily be discontinued if a patient is diagnosed with cardiac valvular disease. In some cases, signs and/or symptoms of cardiac valvulopathy improved after discontinuation of pergolide.

Fibrotic Complications

Case reports have demonstrated that pergolide increases the risk of fibrotic complications including pulmonary, pleural, and/or retroperitoneal fibrosis, pericarditis, pleuritis, and pericardial and/or pleural effusions. Cases have been reported after exposures to pergolide ranging from about one to several years. Precise risk estimates of pergolide-induced fibrotic complications are not available.

Specific risk factors predisposing patients to developing fibrotic complications with pergolide have not been identified. Fibrotic complications have been reported with all therapeutic doses of pergolide.

Pergolide is not recommended for use in patients with a history of fibrotic conditions.

Patients should also be monitored for signs and symptoms of fibrotic complications, including dyspnea, persistent edema, cough, congestive heart failure, new cardiac rub, and/or signs of urinary tract obstruction. If a patient develops these signs or symptoms, consideration should be given to suspending treatment with pergolide until a full diagnostic evaluation has been performed. Pergolide should ordinarily be discontinued if a patient is diagnosed with a specific fibrotic complication. In some cases, signs and/or symptoms of fibrotic complications improved after discontinuation of pergolide.

DESCRIPTION

Permax® (Pergolide Tablets, USP) is an ergot derivative dopamine receptor agonist at both D1 and D2 receptor sites. Pergolide mesylate is chemically designated as 8β-[(Methylthio)methyl]-6-propylergoline monomethanesulfonate; the structural formula is as follows:

The empirical formula is C19H26N2S∙CH4O3S, representing a molecular weight of 410.60.

Permax is provided for oral administration in tablets containing 0.05 mg (0.159 µmol), 0.25 mg (0.795 µmol), or 1 mg (3.18 µmol) pergolide as the base. The tablets also contain croscarmellose sodium, iron oxide, lactose, magnesium stearate, and povidone. The 0.05 mg tablet also contains L-methionine, and the 0.25 mg tablet also contains FD&C Blue No. 2.

CLINICAL PHARMACOLOGY

Pharmacodynamic Information

Pergolide is a potent dopamine receptor agonist. Pergolide is 10 to 1000 times more potent than bromocriptine on a milligram per milligram basis in various in vitro and in vivo test systems. Pergolide inhibits the secretion of prolactin in humans; it causes a transient rise in serum concentrations of growth hormone and a decrease in serum concentrations of luteinizing hormone. In Parkinson's disease, pergolide is believed to exert its therapeutic effect by directly stimulating postsynaptic dopamine receptors in the nigrostriatal system.

Pharmacokinetic Information (Absorption, Distribution, Metabolism, and Elimination)

Information on oral systemic bioavailability of pergolide is unavailable because of the lack of a sufficiently sensitive assay to detect the drug after the administration of a single dose. However, following oral administration of ^14C radiolabeled pergolide, approximately 55% of the administered radioactivity can be recovered from the urine and 5% from expired CO2, suggesting that a significant fraction is absorbed. Nothing can be concluded about the extent of presystemic clearance, if any.

Data on postabsorption distribution of pergolide are unavailable.

At least 10 metabolites have been detected, including N-despropylpergolide, pergolide sulfoxide, and pergolide sulfone. Pergolide sulfoxide and pergolide sulfone are dopamine agonists in animals. The other detected metabolites have not been identified and it is not known whether any other metabolites are active pharmacologically.

The major route of excretion is the kidney.

Pergolide is approximately 90% bound to plasma proteins. This extent of protein binding may be important to consider when pergolide is coadministered with other drugs known to affect protein binding.

INDICATIONS AND USAGE

Permax is indicated as adjunctive treatment to levodopa/carbidopa in the management of the signs and symptoms of Parkinson's disease.

Evidence to support the efficacy of pergolide as an antiparkinsonian adjunct was obtained in a multicenter study enrolling 376 patients with mild to moderate Parkinson's disease who were intolerant to l-dopa/carbidopa as manifested by moderate to severe dyskinesia and/or on-off phenomena. On average, the patients evaluated had been on l-dopa/carbidopa for 3.9 years (range, 2 days to 16.8 years). The administration of pergolide permitted a 5% to 30% reduction in the daily dose of l-dopa. On average, these patients treated with pergolide maintained an equivalent or better clinical status than they exhibited at baseline.

CONTRAINDICATIONS

Pergolide is contraindicated in patients who are hypersensitive to this drug or other ergot derivatives.

WARNINGS

Cardiac Valvulopathy and Fibrotic Complications (SEEBOXED WARNING).

Falling Asleep During Activities of Daily Living—Patients treated with Permax have reported falling asleep while engaged in activities of daily living, including the operation of motor vehicles which sometimes resulted in accidents. Although many of these patients reported somnolence while on Permax, some perceived that they had no warning signs such as excessive drowsiness, and believed that they were alert immediately prior to the event. Some of these events had been reported as late as 1 year after the initiation of treatment.

Somnolence is a common occurrence in patients receiving Permax. Many clinical experts believe that falling asleep while engaged in activities of daily living always occurs in a setting of preexisting somnolence, although patients may not give such a history. For this reason, prescribers should continually reassess patients for drowsiness or sleepiness, especially since some of the events occur well after the start of treatment. Prescribers should also be aware that patients may not acknowledge drowsiness or sleepiness until directly questioned about drowsiness or sleepiness during specific activities.

Before initiating treatment with Permax, patients should be advised of the potential to develop drowsiness and specifically asked about factors that may increase the risk with Permax such as concomitant sedating medications or the presence of sleep disorders. If a patient develops significant daytime sleepiness or episodes of falling asleep during activities that require participation (e.g., conversations, eating, etc.), Permax should ordinarily be discontinued. If a decision is made to continue Permax, patients should be advised to not drive and to avoid other potentially dangerous activities.

While dose reduction may reduce the degree of somnolence, there is insufficient information to establish that dose reduction will eliminate episodes of falling asleep while engaged in activities of daily living.

Symptomatic Hypotension — In clinical trials, approximately 10% of patients taking pergolide with l-dopa versus 7% taking placebo with l-dopa experienced symptomatic orthostatic and/or sustained hypotension, especially during initial treatment. With gradual dosage titration, tolerance to the hypotension usually develops. It is therefore important to warn patients of the risk, to begin therapy with low doses, and to increase the dosage in carefully adjusted increments over a period of 3 to 4 weeks (seeDOSAGE AND ADMINISTRATION).

Hallucinosis— In controlled trials, pergolide with l-dopa caused hallucinosis in about 14% of patients as opposed to 3% taking placebo with l-dopa. This was of sufficient severity to cause discontinuation of treatment in about 3% of those enrolled; tolerance to this untoward effect was not observed.

Fatalities— In the placebo-controlled trial, 2 of 187 patients treated with placebo died as compared with 1 of 189 patients treated with pergolide. Of the 2299 patients treated with pergolide in premarketing studies evaluated as of October 1988, 143 died while on the drug or shortly after discontinuing it. Because the patient population under evaluation was elderly, ill, and at high risk for death, it seems unlikely that pergolide played any role in these deaths, but the possibility that pergolide shortens survival of patients cannot be excluded with absolute certainty.

In particular, a case-by-case review of the clinical course of the patients who died failed to disclose any unique set of signs, symptoms, or laboratory results that would suggest that treatment with pergolide caused their deaths. Sixty-eight percent (68%) of the patients who died were 65 years of age or older. No death (other than a suicide) occurred within the first month of treatment; most of the patients who died had been on pergolide for years. A relative frequency of the causes of death by organ system are: Pulmonary failure/Pneumonia, 35%; Cardiovascular, 30%; Cancer, 11%; Unknown, 8.4%; Infection, 3.5%; Extrapyramidal syndrome, 3.5%; Stroke, 2.1%; Dysphagia, 2.1%; Injury, 1.4%; Suicide, 1.4%; Dehydration, 0.7%; Glomerulonephritis, 0.7%.

PRECAUTIONS

General

Caution should be exercised when administering pergolide to patients prone to cardiac dysrhythmias.

In a study comparing pergolide and placebo, patients taking pergolide were found to have significantly more episodes of atrial premature contractions (APCs) and sinus tachycardia.

The use of pergolide in patients on l-dopa may cause and/or exacerbate preexisting states of confusion and hallucinations (seeWARNINGS) and preexisting dyskinesia. Also, the abrupt discontinuation of pergolide in patients receiving it chronically as an adjunct to l-dopa may precipitate the onset of hallucinations and confusion; these may occur within a span of several days. Discontinuation of pergolide should be undertaken gradually whenever possible, even if the patient is to remain on l-dopa.

A symptom complex resembling the neuroleptic malignant syndrome (NMS) (characterized by elevated temperature, muscular rigidity, altered consciousness, and autonomic instability), with no other obvious etiology, has been reported in association with rapid dose reduction, withdrawal of, or changes in antiparkinsonian therapy, including pergolide.

Raynaud’s Phenomenon

Pergolide can rarely cause Raynaud’s phenomenon.

Information for Patients

Because pergolide may cause somnolence and the possibility of falling asleep during activities of daily living, patients should be cautioned about operating hazardous machinery, including automobiles, until they are reasonably certain that pergolide therapy does not affect them adversely. Patients should be advised that if increased somnolence or new episodes of falling asleep during activities of daily living (e.g., watching television, passenger in a car, etc.) are experienced at any time during treatment, they should not drive or participate in potentially dangerous activities until they have contacted their physician. Due to the possible additive sedative effects, caution should also be used when patients are taking other CNS depressants in combination with pergolide.

Patients and their families should be informed of the common adverse consequences of the use of pergolide (seeADVERSE REACTIONS) and the risk of hypotension (seeWARNINGS).

Patients should be advised to notify their physician if they become pregnant or intend to become pregnant during therapy.

Patients should be advised to notify their physician if they are breast feeding an infant.

As with other dopamine agonists, compulsive self-rewarding behavior (e.g., pathologic gambling) and libido increase have been reported in patients receiving pergolide therapy.

Laboratory Tests

No specific laboratory tests are deemed essential for the management of patients on Permax. Periodic routine evaluation of all patients, however, is appropriate.

Drug Interactions

Dopamine antagonists, such as the neuroleptics (phenothiazines, butyrophenones, thioxanthines) or metoclopramide, ordinarily should not be administered concurrently with Permax (a dopamine agonist); these agents may diminish the effectiveness of Permax.

Because pergolide is approximately 90% bound to plasma proteins, caution should be exercised if pergolide is coadministered with other drugs known to affect protein binding.

Carcinogenesis, Mutagenesis, Impairment of Fertility

A 2-year carcinogenicity study was conducted in mice using dietary levels of pergolide equivalent to oral doses of 0.6, 3.7, and 36.4 mg/kg/day in males and 0.6, 4.4, and 40.8 mg/kg/day in females. A 2-year study in rats was conducted using dietary levels equivalent to oral doses of 0.04, 0.18, and 0.88 mg/kg/day in males and 0.05, 0.28, and 1.42 mg/kg/day in females. The highest doses tested in the mice and rats were approximately 340 and 12 times the maximum human oral dose administered in controlled clinical trials (6 mg/day equivalent to 0.12 mg/kg/day).

A low incidence of uterine neoplasms occurred in both rats and mice. Endometrial adenomas and carcinomas were observed in rats. Endometrial sarcomas were observed in mice. The occurrence of these neoplasms is probably attributable to the high estrogen/progesterone ratio that would occur in rodents as a result of the prolactin-inhibiting action of pergolide. The endocrine mechanisms believed to be involved in the rodents are not present in humans. However, even though there is no known correlation between uterine malignancies occurring in pergolide-treated rodents and human risk, there are no human data to substantiate this conclusion.

Pergolide was evaluated for mutagenic potential in a battery of tests that included an Ames bacterial mutation assay, a DNA repair assay in cultured rat hepatocytes, an in vitro mammalian cell gene mutation assay in cultured L5178Y cells, and a determination of chromosome alteration in bone marrow cells of Chinese hamsters. A weak mutagenic response was noted in the mammalian cell gene mutation assay only after metabolic activation with rat liver microsomes. No mutagenic effects were obtained in the 2 other in vitro assays and in the in vivo assay. The relevance of these findings in humans is unknown.

A fertility study in male and female mice showed that fertility was maintained at 0.6 and 1.7 mg/kg/day but decreased at 5.6 mg/kg/day. Prolactin has been reported to be involved in stimulating and maintaining progesterone levels required for implantation in mice and, therefore, the impaired fertility at the high dose may have occurred because of depressed prolactin levels.

Usage in Pregnancy − Pregnancy Category B

Reproduction studies were conducted in mice at doses of 5, 16, and 45 mg/kg/day and in rabbits at doses of 2, 6, and 16 mg/kg/day. The highest doses tested in mice and rabbits were 375 and 133 times the 6 mg/day maximum human dose administered in controlled clinical trials. In these studies, there was no evidence of harm to the fetus due to pergolide.

There are, however, no adequate and well-controlled studies in pregnant women. Among women who received pergolide for endocrine disorders in premarketing studies, there were 33 pregnancies that resulted in healthy babies and 6 pregnancies that resulted in congenital abnormalities (3 major, 3 minor); a causal relationship has not been established. Because human data are limited and because animal reproduction studies are not always predictive of human response, this drug should be used during pregnancy only if clearly needed.

Nursing Mothers

It is not known whether this drug is excreted in human milk. The pharmacologic action of pergolide suggests that it may interfere with lactation. Because many drugs are excreted in human milk and because of the potential for serious adverse reactions to pergolide in nursing infants, a decision should be made whether to discontinue nursing or to discontinue the drug, taking into account the importance of the drug to the mother.

Pediatric Use

Safety and effectiveness in pediatric patients have not been established.

Geriatric Use

Of the total number of subjects in clinical studies of pergolide, 78 were 65 and over. There were no apparent differences in efficacy between these subjects and younger subjects. There was an increased incidence of confusion, somnolence, and peripheral edema in patients 65 and over. Other reported clinical experience has not identified differences in responses between the elderly and younger patients, but greater sensitivity of some older individuals cannot be ruled out. This drug is known to be substantially excreted by the kidney, and the risk of toxic reactions to this drug may be greater in patients with impaired renal function. Because elderly patients are more likely to have decreased renal function, care should be taken in dose selection, and it may be useful to monitor renal function.

ADVERSE REACTIONS

Commonly Observed— In premarketing clinical trials, the most commonly observed adverse events associated with use of pergolide which were not seen at an equivalent incidence among placebo-treated patients were: nervous system complaints, including dyskinesia, hallucinations, somnolence, insomnia; digestive complaints, including nausea, constipation, diarrhea, dyspepsia; and respiratory system complaints, including rhinitis.

Associated With Discontinuation of Treatment— Twenty-seven percent (27%) of approximately 1200 patients receiving pergolide for treatment of Parkinson's disease in premarketing clinical trials in the US and Canada discontinued treatment due to adverse events. The events most commonly causing discontinuation were related to the nervous system (15.5%), primarily hallucinations (7.8%) and confusion (1.8%).

Fatalities —seeWARNINGS

Incidence in Controlled Clinical Trials— The table that follows enumerates adverse events that occurred at a frequency of 1% or more among patients taking pergolide who participated in the premarketing controlled clinical trials comparing pergolide with placebo. In a double-blind, controlled study of 6 months’ duration, patients with Parkinson’s disease were continued on l-dopa/carbidopa and were randomly assigned to receive either pergolide or placebo as additional therapy.

The prescriber should be aware that these figures cannot be used to predict the incidence of side effects in the course of usual medical practice where patient characteristics and other factors differ from those which prevailed in the clinical trials. Similarly, the cited frequencies cannot be compared with figures obtained from other clinical investigations involving different treatments, uses, and investigators. The cited figures, however, do provide the prescribing physician with some basis for estimating the relative contribution of drug and nondrug factors to the side-effect incidence rate in the population studied.

Incidence of Treatment-Emergent Adverse Experiences in the Placebo-Controlled Clinical Trial
 | Percentage of Patients Reporting Events
 | Pergolide | Placebo
Body system/Adverse Event* | N=189 | N=187
Body as a Whole
Pain | 7.0 | 2.1
Abdominal pain | 5.8 | 2.1
Injury, accident | 5.8 | 7.0
Headache | 5.3 | 6.4
Asthenia | 4.2 | 4.8
Chest pain | 3.7 | 2.1
Flu syndrome | 3.2 | 2.1
Neck pain | 2.7 | 1.6
Back pain | 1.6 | 2.1
Surgical procedure | 1.6 | <1
Chills | 1.1 | 0
Face edema | 1.1 | 0
Infection | 1.1 | 0
Cardiovascular
Postural hypotension | 9.0 | 7.0
Vasodilatation | 3.2 | <1
Palpitation | 2.1 | <1
Hypotension | 2.1 | <1
Syncope | 2.1 | 1.1
Hypertension | 1.6 | 1.1
Arrhythmia | 1.1 | <1
Myocardial infarction | 1.1 | <1
Digestive
Nausea | 24.3 | 12.8
Constipation | 10.6 | 5.9
Diarrhea | 6.4 | 2.7
Dyspepsia | 6.4 | 2.1
Anorexia | 4.8 | 2.7
Dry mouth | 3.7 | <1
Vomitting | 2.7 | 1.6
Hemic and Lymphatic
Anemia | 1.1 | <1
Metabolic and Nutritional
Peripheral edema | 7.4 | 4.3
Edema | 1.6 | 0
Weight gain | 1.6 | 0
Musuloskeletal
Arthralgia | 1.6 | 2.1
Bursitis | 1.6 | <1
Myalgia | 1.1 | <1
Twitching | 1.1 | 0
Nervous System
Dyskinesia | 62.4 | 24.6
Dizziness | 19.1 | 13.9
Hallucinations | 13.8 | 3.2
Dystonia | 11.6 | 8.0
Confusion | 11.1 | 9.6
Somnolence | 10.1 | 3.7
Insomnia | 7.9 | 3.2
Anxiety | 6.4 | 4.3
Tremor | 4.2 | 7.5
Depression | 3.2 | 5.4
Abnormal dreams | 2.7 | 4.3
Personality disorder | 2.1 | <1
Psychosis | 2.1 | 0
Abnormal gait | 1.6 | 1.6
Akathisia | 1.6 | 0
Extrapyramidal syndrome | 1.6 | 1.1
Incoordination | 1.6 | <1
Paresthesia | 1.6 | 3.2
Akinesia | 1.1 | 1.1
Hypertonia | 1.1 | 0
Neuralgia | 1.1 | <1
Speech disorder | 1.1 | 1.6
Respiratory system
Rhinitis | 12.2 | 5.4
Dyspnea | 4.8 | 1.1
Epistaxis | 1.6 | <1
Hiccup | 1.1 | 0
Skin and Appendages
Rash | 3.2 | 2.1
Sweating | 2.1 | 2.7
Special Senses
Abnormal vision | 5.8 | 5.4
Diplopia | 2.1 | 0
Taste perversion | 1.6 | 0
Eye disorder | 1.1 | 0
Urogenital System
Urinary frequency | 2.7 | 6.4
Urinary tract infection | 2.7 | 3.7
Hematuria | 1.1 | <1
*Events reported by at least 1% of patients receiving pergolide are included.

Events Observed During the Premarketing Evaluation of Permax— This section reports event frequencies evaluated as of October 1988 for adverse events occurring in a group of approximately 1800 patients who took multiple doses of pergolide. The conditions and duration of exposure to pergolide varied greatly, involving well-controlled studies as well as experience in open and uncontrolled clinical settings. In the absence of appropriate controls in some of the studies, a causal relationship between these events and treatment with pergolide cannot be determined.

The following enumeration by organ system describes events in terms of their relative frequency of reporting in the data base. Events of major clinical importance are also described in the Warnings and Precautions sections.

The following definitions of frequency are used: frequent adverse events are defined as those occurring in at least 1/100 patients; infrequent adverse events are those occurring in 1/100 to 1/1000 patients; rare events are those occurring in fewer than 1/1000 patients.

Body as a Whole—Frequent: headache, asthenia, accidental injury, pain, abdominal pain, chest pain, back pain, flu syndrome, neck pain, fever; Infrequent: facial edema, chills, enlarged abdomen, malaise, neoplasm, hernia, pelvic pain, sepsis, cellulitis, moniliasis, abscess, jaw pain, hypothermia; Rare: acute abdominal syndrome, LE syndrome.

Cardiovascular System—Frequent: postural hypotension, syncope, hypertension, palpitations, vasodilatations, congestive heart failure; Infrequent: myocardial infarction, tachycardia, heart arrest, abnormal electrocardiogram, angina pectoris, thrombophlebitis, bradycardia, ventricular extrasystoles, cerebrovascular accident, ventricular tachycardia, cerebral ischemia, atrial fibrillation, varicose vein, pulmonary embolus, AV block, shock; Rare: vasculitis, pulmonary hypertension, pericarditis, migraine, heart block, cerebral hemorrhage.

Digestive System—Frequent: nausea, vomiting, dyspepsia, diarrhea, constipation, dry mouth, dysphagia; Infrequent: flatulence, abnormal liver function tests, increased appetite, salivary gland enlargement, thirst, gastroenteritis, gastritis, periodontal abscess, intestinal obstruction, nausea and vomiting, gingivitis, esophagitis, cholelithiasis, tooth caries, hepatitis, stomach ulcer, melena, hepatomegaly, hematemesis, eructation; Rare: sialadenitis, peptic ulcer, pancreatitis, jaundice, glossitis, fecal incontinence, duodenitis, colitis, cholecystitis, aphthous stomatitis, esophageal ulcer.

Endocrine System—Infrequent: hypothyroidism, adenoma, diabetes mellitus, ADH inappropriate; Rare: endocrine disorder, thyroid adenoma.

Hemic and Lymphatic System—Frequent: anemia; Infrequent: leukopenia, lymphadenopathy, leukocytosis, thrombocytopenia, petechia, megaloblastic anemia, cyanosis; Rare: purpura, lymphocytosis, eosinophilia, thrombocythemia, acute lymphoblastic leukemia, polycythemia, splenomegaly.

Metabolic and Nutritional System—Frequent: peripheral edema, weight loss, weight gain; Infrequent: dehydration, hypokalemia, hypoglycemia, iron deficiency anemia, hyperglycemia, gout, hypercholesteremia; Rare: electrolyte imbalance, cachexia, acidosis, hyperuricemia.

Musculoskeletal System—Frequent: twitching, myalgia, arthralgia; Infrequent: bone pain, tenosynovitis, myositis, bone sarcoma, arthritis; Rare: osteoporosis, muscle atrophy, osteomyelitis.

Nervous System—Frequent: dyskinesia, dizziness, hallucinations, confusion, somnolence, insomnia, dystonia, paresthesia, depression, anxiety, tremor, akinesia, extrapyramidal syndrome, abnormal gait, abnormal dreams, incoordination, psychosis, personality disorder, nervousness, choreoathetosis, amnesia, paranoid reaction, abnormal thinking; Infrequent: akathisia, neuropathy, neuralgia, hypertonia, delusions, convulsion, libido increased, euphoria, emotional lability, libido decreased, vertigo, myoclonus, coma, apathy, paralysis, neurosis, hyperkinesia, ataxia, acute brain syndrome, torticollis, meningitis, manic reaction, hypokinesia, hostility, agitation, hypotonia; Rare: stupor, neuritis, intracranial hypertension, hemiplegia, facial paralysis, brain edema, myelitis, hallucinations and confusion after abrupt discontinuation.

Respiratory System—Frequent: rhinitis, dyspnea, pneumonia, pharyngitis, cough increased; Infrequent: epistaxis, hiccup, sinusitis, bronchitis, voice alteration, hemoptysis, asthma, lung edema, pleural effusion, laryngitis, emphysema, apnea, hyperventilation; Rare: pneumothorax, lung fibrosis, larynx edema, hypoxia, hypoventilation, hemothorax, carcinoma of lung.

Skin and Appendages System—Frequent: sweating, rash; Infrequent: skin discoloration, pruritus, acne, skin ulcer, alopecia, dry skin, skin carcinoma, seborrhea, hirsutism, herpes simplex, eczema, fungal dermatitis, herpes zoster; Rare: vesiculobullous rash, subcutaneous nodule, skin nodule, skin benign neoplasm, lichenoid dermatitis.

Special Senses System—Frequent: abnormal vision, diplopia; Infrequent: otitis media, conjunctivitis, tinnitus, deafness, taste perversion, ear pain, eye pain, glaucoma, eye hemorrhage, photophobia, visual field defect; Rare: blindness, cataract, retinal detachment, retinal vascular disorder.

Urogenital System—Frequent: urinary tract infection, urinary frequency, urinary incontinence, hematuria, dysmenorrhea; Infrequent: dysuria, breast pain, menorrhagia, impotence, cystitis, urinary retention, abortion, vaginal hemorrhage, vaginitis, priapism, kidney calculus, fibrocystic breast, lactation, uterine hemorrhage, urolithiasis, salpingitis, pyuria, metrorrhagia, menopause, kidney failure, breast carcinoma, cervical carcinoma; Rare: amenorrhea, bladder carcinoma, breast engorgement, epididymitis, hypogonadism, leukorrhea, nephrosis, pyelonephritis, urethral pain, uricaciduria, withdrawal bleeding.

Postintroduction Reports— Voluntary reports of adverse events temporally associated with pergolide that have been received since market introduction and which may have no causal relationship with the drug, include the following: neuroleptic malignant syndrome and Raynaud’s phenomenon.

OVERDOSAGE

There is no clinical experience with massive overdosage. The largest overdose involved a young hospitalized adult patient who was not being treated with pergolide but who intentionally took 60 mg of the drug. He experienced vomiting, hypotension, and agitation. Another patient receiving a daily dosage of 7 mg of pergolide unintentionally took 19 mg/day for 3 days, after which his vital signs were normal but he experienced severe hallucinations. Within 36 hours of resumption of the prescribed dosage level, the hallucinations stopped. One patient unintentionally took 14 mg/day for 23 days instead of her prescribed 1.4 mg/day dosage. She experienced severe involuntary movements and tingling in her arms and legs. Another patient who inadvertently received 7 mg instead of the prescribed 0.7 mg experienced palpitations, hypotension, and ventricular extrasystoles. The highest total daily dose (prescribed for several patients with refractory Parkinson's disease) has exceeded 30 mg.

Symptoms— Animal studies indicate that the manifestations of overdosage in man might include nausea, vomiting, convulsions, decreased blood pressure, and CNS stimulation. The oral median lethal doses in mice and rats were 54 and 15 mg/kg respectively.

Treatment— To obtain up-to-date information about the treatment of overdose, a good resource is your certified Regional Poison Control Center. Telephone numbers of certified poison control centers are listed in the Physicians’ Desk Reference (PDR). In managing overdosage, consider the possibility of multiple drug overdoses, interaction among drugs, and unusual drug kinetics in your patient.

Management of overdosage may require supportive measures to maintain arterial blood pressure. Cardiac function should be monitored; an antiarrhythmic agent may be necessary. If signs of CNS stimulation are present, a phenothiazine or other butyrophenone neuroleptic agent may be indicated; the efficacy of such drugs in reversing the effects of overdose has not been assessed.

Protect the patient’s airway and support ventilation and perfusion. Meticulously monitor and maintain, within acceptable limits, the patient’s vital signs, blood gases, serum electrolytes, etc. Absorption of drugs from the gastrointestinal tract may be decreased by giving activated charcoal, which, in many cases, is more effective than emesis or lavage; consider charcoal instead of or in addition to gastric emptying. Repeated doses of charcoal over time may hasten elimination of some drugs that have been absorbed. Safeguard the patient’s airway when employing gastric emptying or charcoal.

There is no experience with dialysis or hemoperfusion, and these procedures are unlikely to be of benefit.

DOSAGE AND ADMINISTRATION

Administration of Permax should be initiated with a daily dosage of 0.05 mg for the first 2 days. The dosage should then be gradually increased by 0.1 or 0.15 mg/day every third day over the next 12 days of therapy. The dosage may then be increased by 0.25 mg/day every third day until an optimal therapeutic dosage is achieved.

Permax is usually administered in divided doses 3 times per day. During dosage titration, the dosage of concurrent l-dopa/carbidopa may be cautiously decreased.

In clinical studies, the mean therapeutic daily dosage of Permax was 3 mg/day. The average concurrent daily dosage of l-dopa/carbidopa (expressed as l-dopa) was approximately 650 mg/day. The efficacy of Permax at doses above 5 mg/day has not been systematically evaluated. Doses of pergolide above 5 mg/day are not recommended (seeWARNINGS).

HOW SUPPLIED

Tablets (modified rectangle shape, scored):

0.05 mg, ivory, debossed with A 024, in bottles of 30 (UC5336) — NDC 0187-0839-01

0.25 mg, green, debossed with A 025, in bottles of 100 (UC5337) — NDC 0187-0840-02

1 mg, pink, debossed with A 026, in bottles of 100 (UC5338) — NDC 0187-0841-02

Store at 25°C (77°F); excursions permitted to 15°C-30°C (59°F-86°F) [see USP Controlled Room Temperature].

PERMAX is a registered trademark of Eli Lilly and Company, and licensed in the US to Valeant Pharmaceuticals International.

Literature revised August 18, 2004

Manufactured for:
Valeant Pharmaceuticals International
3300 Hyland Ave.
Costa Mesa, CA 92626 U.S.A.

Part Number 3083900EX00
PRINTED IN USA